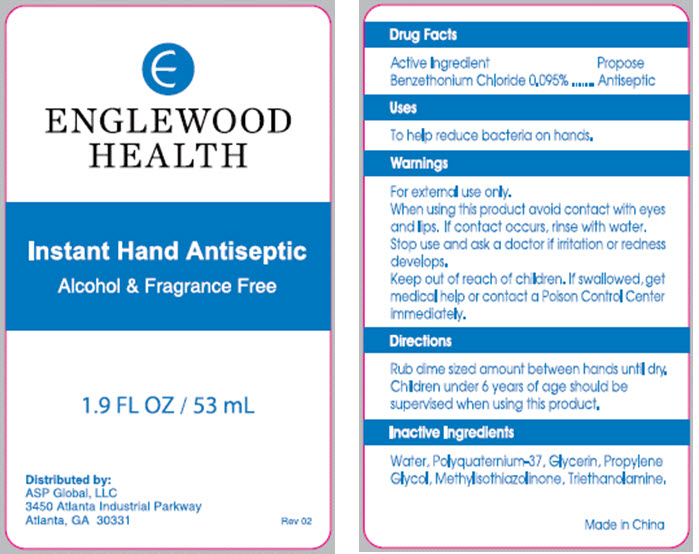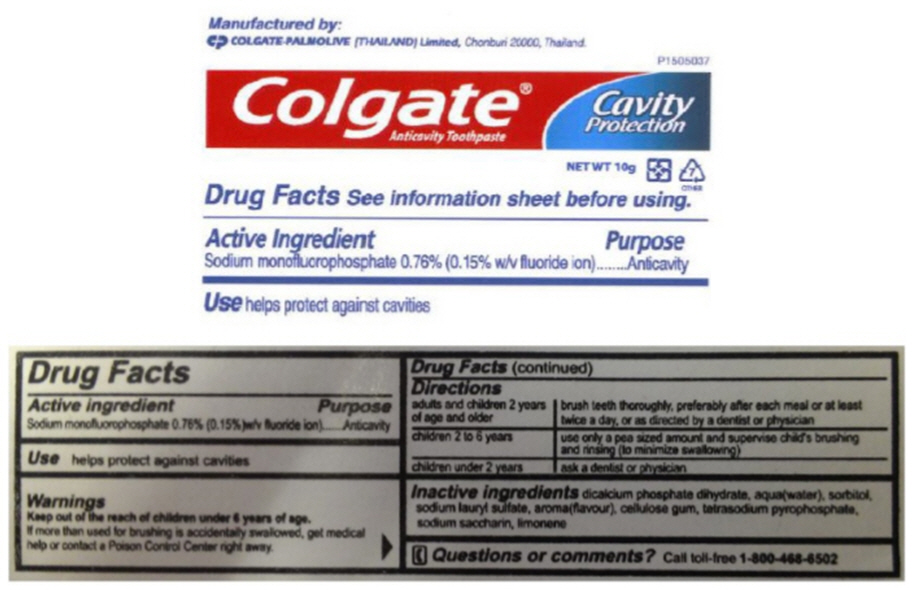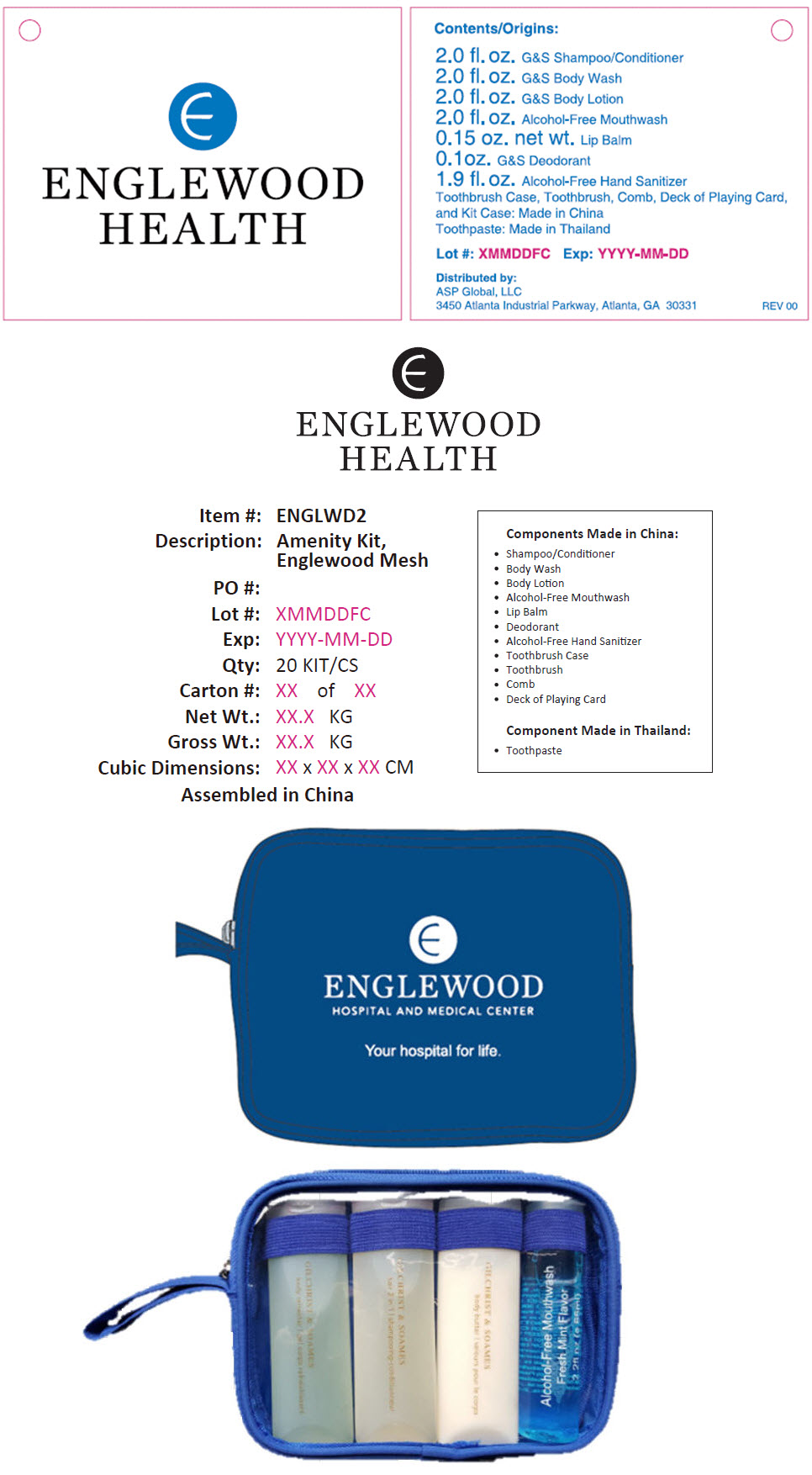 DRUG LABEL: Englewood Mesh Amenity
NDC: 59448-401 | Form: KIT | Route: TOPICAL
Manufacturer: ASP Global, LLc
Category: otc | Type: HUMAN OTC DRUG LABEL
Date: 20251229

ACTIVE INGREDIENTS: Benzalkonium Chloride 0.095 mg/100 mL; SODIUM MONOFLUOROPHOSPHATE 7.6 mg/1 g
INACTIVE INGREDIENTS: Water; POLYQUATERNIUM-37 (25000 MPA.S); Glycerin; Propylene Glycol; Methylisothiazolinone; Trolamine; DIBASIC CALCIUM PHOSPHATE DIHYDRATE; Water; Sorbitol; Sodium Lauryl Sulfate; SODIUM PYROPHOSPHATE; SACCHARIN SODIUM

Englewood Mesh Amenity Kit

Instant Hand Antiseptic

Drug Facts

Active Ingredient

Benzalkonium Chloride 0.095%

Propose

Antiseptic

Uses

To help reduce bacteria on hands.

Warnings

For external use only.

When using this product avoid contact with eyes and lips. If contact occurs, rinse with water.

Stop use and ask a doctor if irritation or redness develops.

Keep out of reach of children. If swallowed, get medical help or contact a Poison Control Center immediately.

Directions

Rub dime sized amount between hands until dry.

Children under 6 years of age should be supervised when using this product.

Inactive Ingredients

Water, Polyquaternium-37, Glycerin, Propylene Glycol, Methylisothiazolinone, Trithanolamine.

Distributed by:
ASP Global, LLC
3450 Atlanta Industrial Parkway
Atlanta, GA 30331

Colgate® Anticavity Toothpaste

Drug Facts

Active Ingredient

Sodium monofluorophosphate 0.76% (0.15% w/v fluoride ion)

Purpose

Anticavity

Use

helps protect against cavities

Warnings

KEEP OUT OF REACH OF CHILDREN

Keep out of the reach of children under 6 years of age.

If more than used for brushing is accidentally swallowed, get medical help or contact a Poison Control Center right away.

Directions

adults and children 2 years of age and older | brush teeth thoroughly, preferably after each meal or at least twice a day, or as directed by a dentist or physician
children 2 to 6 years | use only a pea sized amount and supervise child's brushing and rinsing (to minimize swallowing)
children under 2 years | ask a dentist or physician

Inactive ingredients

dicalcium phosphate dihydrate, aqua(water), sorbitol, sodium lauryl sulfate, aroma(flavour), cellulose gum, tetrasodium pyrophosphate, sodium saccharin, limonene

Questions or comments?

Call toll-free 1-800-468-6502

Manufactured by:

COLGATE-PALMOLIVE (THAILAND) Limited, Chonburi 20000, Thailand.

PRINCIPAL DISPLAY PANEL - 53 mL Bottle Label

ENGLEWOOD
HEALTH

Instant Hand Antiseptic

Alcohol & Fragrance Free

1.9 FL OZ / 53 mL

Distributed by:
ASP Global, LLC
3450 Atlanta Industrial Parkway
Atlanta, GA 30331
Rev 02

PRINCIPAL DISPLAY PANEL - 10 g Tube Label

P1505037

Colgate®
Anticavity Toothpaste

Cavity
Protection

NET WT 10g
7
OTHER

PRINCIPAL DISPLAY PANEL - Kit Label

ENGLEWOOD
HEALTH

Contents/Origins:

2.0 fl. oz. G&S Shampoo/Conditioner
2.0 fl. oz. G&S Body Wash
2.0 fl. oz. G&S Body Lotion
2.0 fl. oz. Alcohol-Free Mouthwash
0.15 oz. net wt. Lip Balm
0.1oz. G&S Deodorant
1.9 fl. oz. Alcohol-Free Hand Sanitizer
Toothbrush Case, Toothbrush, Comb, Deck of Playing Card,
and Kit Case: Made in China
Toothpaste: Made in Thailand

Lot #: XMMDDFC Exp: YYYY-MM-DD

Distributed by:
ASP Global, LLC
3450 Atlanta Industrial Parkway, Atlanta, GA 30331
REV 00

ENGLEWOOD
HEALTH

Item #: ENGLWD2
Description: Amenity Kit,
Englewood Mesh

PO #:
Lot #: XMMDDFC
Exp: YYYY-MM-DD
Qty: 20 KIT/CS
Carton #: XX of XX
Net Wt.: XX.X KG
Gross Wt.: XX.X KG
Cubic Dimensions: XX x XX x XX CM

Assembled in China

Components Made in China:

- Shampoo/Conditioner
- Body Wash
- Body Lotion
- Alcohol-Free Mouthwash
- Lip Balm
- Deodorant
- Alcohol-Free Hand Sanitizer
- Toothbrush Case
- Toothbrush
- Comb
- Deck of Playing Card

Component Made in Thailand:

- Toothpaste

ENGLEWOOD
HOSPITAL AND MEDICAL CENTER

Your hospital for life.